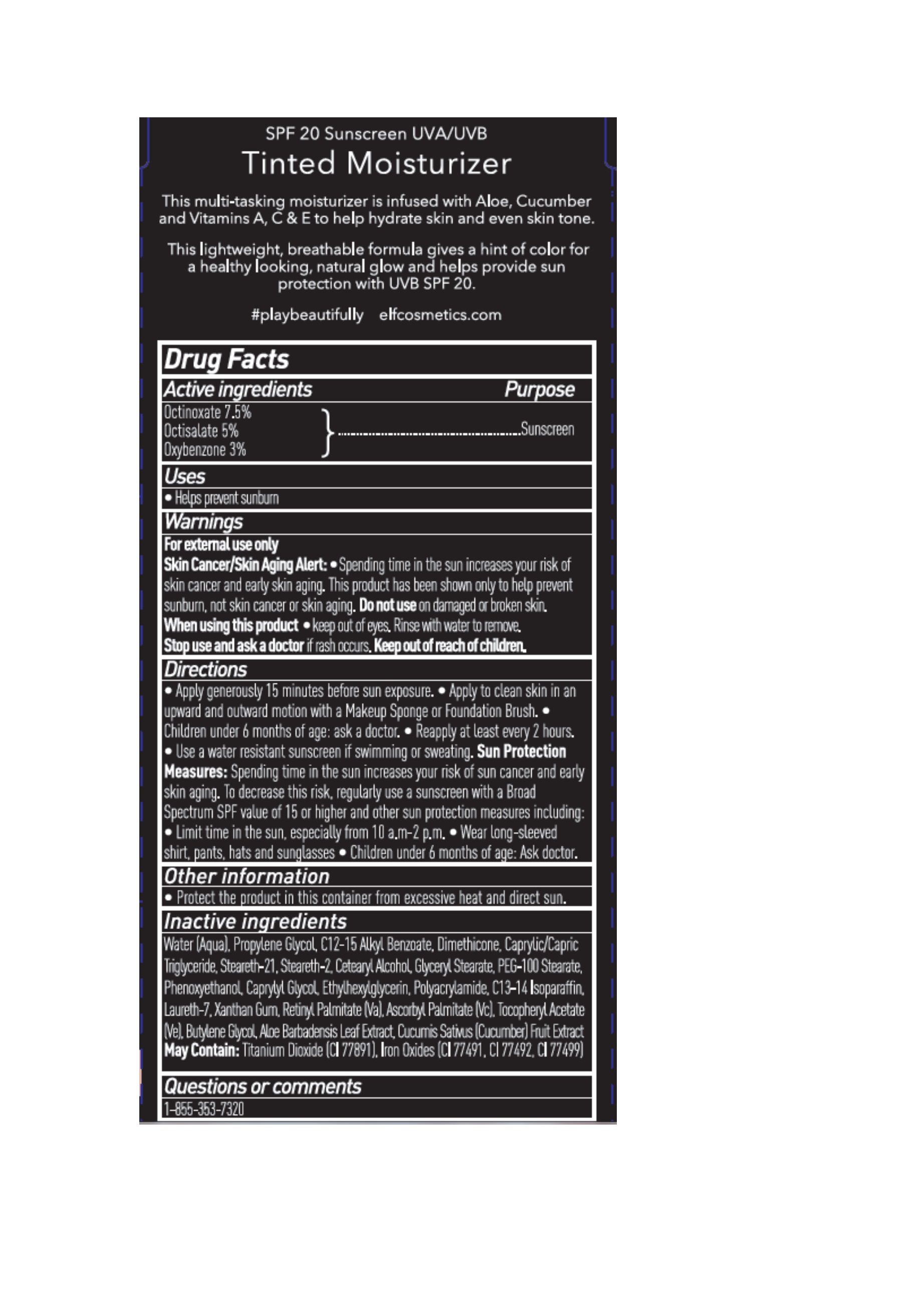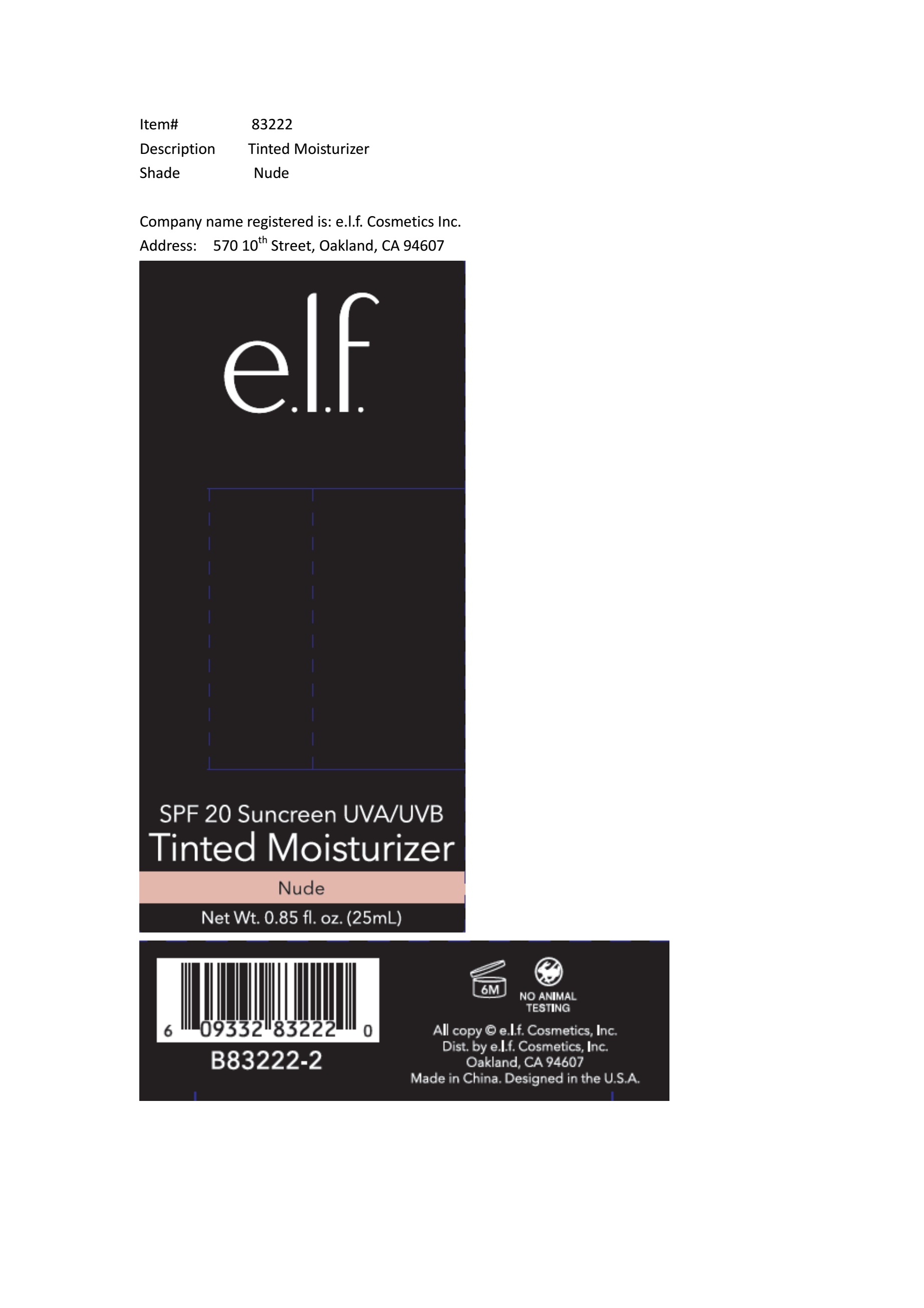 DRUG LABEL: SPF 20 Sunscreen UVAUVB Tinted Moisturizer Nude
NDC: 52664-633 | Form: CREAM
Manufacturer: Hangzhou Facecare Cosmetics Co., Ltd.
Category: otc | Type: HUMAN OTC DRUG LABEL
Date: 20201210

ACTIVE INGREDIENTS: OCTISALATE 5 g/100 mL; OCTINOXATE 7.5 g/100 mL; OXYBENZONE 3 g/100 mL
INACTIVE INGREDIENTS: WATER; FERRIC OXIDE RED; FERRIC OXIDE YELLOW; FERROSOFERRIC OXIDE; PROPYLENE GLYCOL; TITANIUM DIOXIDE; DIMETHICONE; STEARETH-21; PEG-100 STEARATE; PHENOXYETHANOL; CAPRYLYL GLYCOL; ETHYLHEXYLGLYCERIN; POLYACRYLAMIDE (1500 MW); C13-14 ISOPARAFFIN; LAURETH-7; XANTHAN GUM; VITAMIN A; ASCORBYL PALMITATE; .ALPHA.-TOCOPHEROL ACETATE; BUTYLENE GLYCOL; CUCUMIS SATIVUS WHOLE; STEARETH-2; GLYCERYL STEARATE SE

Drug Fact

Active Ingredient:

Octinoxate: 7.5%

Octisalate: 5%

Oxybenzone: 3%

Purpose:

Sunscreen

Uses:

Helps prevent sunburn

Warning:

For external use only

Skin Cancer/ Skin Aging Alert: Spending time in the sun increases your risk of skin cancer or early skin aging. This product has been shown to only protect you from sunburn, not skin cancer or sking aging.

Do not use on damage or broken skin

When using this product:

Keep out of eyes. Rinse with water to remove.

Stop Use and Ask a Doctor if r ash occurs

Keep Out of Reach of Children

Directions:

For sunscreen use:

Apply generously 15 min before sun exposure.

Apply to clean skin in an upward and outward motion with sponage or foundation brush

Children under six months of age: ask a doctor.

Reapply at least every two hours.

Use a water resistant sunscreen if swimming or sweating

Sun Protection Measures:

Spending time in sun increases your risk of skin cancer or early skin aging. To decrease the risk, regularly use a sunscreen with broad spectrum SPF value of 15 or higher and other sun protection measures including

- Limit time in the sun, especially from 10 am to 2 pm
- Wear long sleeved shirts, pants, hats, and sunglasses.
- Children under six months of age: ask a doctor

Other Information:

Protect this product in the container from excessive heat and direct sun

Store at room temperature 15-30 C (59-86F)

Inactive Ingredient:

Water, Dimethicone, Propylene Glycol, C12-15 Alkyl Benzoate, Caprylic/Capric Triglyceride, Steareth-21, Steareth-2, Cetearyl Alcohol, Glyceryl Stearate, PEG-100 Stearate, Phenoxyethanol, Caprylyl Glycol, Ethylhexyglycerin, Polyacrylamide, C13-14 Isoparaffin, Laureth-7, Xantahn Gum, Retinyl Palmitate (VA), Ascorbyl Palmitate (VC), Tocopheryl Acetate (VE), Butylene Glycol, Aloe Barbadensis Leaf Extract, Cucumis Sativus (Cucumber) Fruit Extract

May contain:

Titanium Oxide, Iron Oxides (CI 77491, CI 77492, CI 77499)